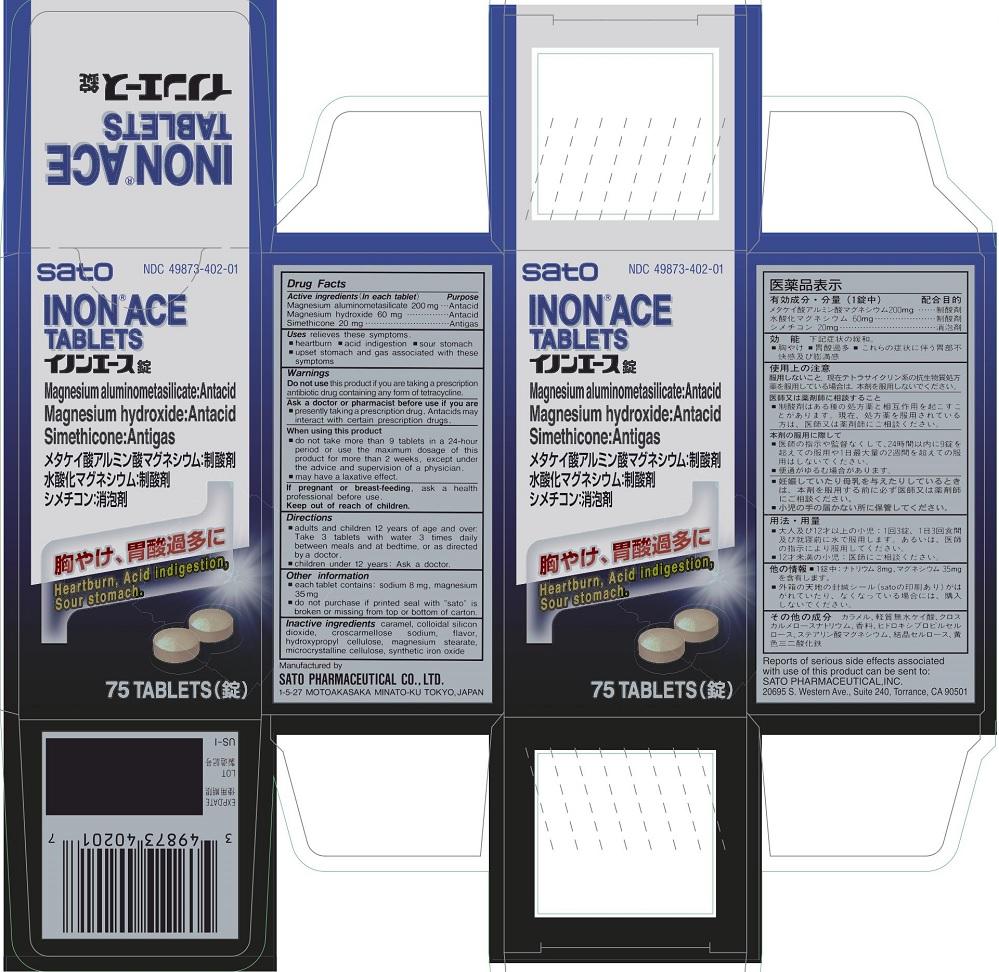 DRUG LABEL: Inon Ace
NDC: 49873-402 | Form: TABLET
Manufacturer: Sato Pharmaceutical Co., Ltd.
Category: otc | Type: HUMAN OTC DRUG LABEL
Date: 20231110

ACTIVE INGREDIENTS: MAGNESIUM HYDROXIDE 60 mg/1 1; SILODRATE 200 mg/1 1; DIMETHICONE 20 mg/1 1
INACTIVE INGREDIENTS: CARAMEL; SILICON DIOXIDE; CROSCARMELLOSE SODIUM; HYDROXYPROPYL CELLULOSE; MAGNESIUM STEARATE; CELLULOSE, MICROCRYSTALLINE; FERRIC OXIDE YELLOW

Inon Ace Tablets

Active ingredients (in each tablet)
Magnesium Aluminosilicates 200 mg
Magnesium Hydroxide 60 mg
Simethicone 20 mg

Purposes
Magnesium Aluminosilicates Antacid
Magnesium Hydroxide Antacid
Simethicone Antigas

INDICATIONS AND USAGE

Uses relieves these symptoms
■heartburn ■acid indigestion ■sour stomach
■upset stomach and gas associated with these symptoms

WARNINGS

Enter section text here

Ask a doctor or pharmacist before use if you are
■taking a prescription drug. Antacids may interact with certain prescription drugs

When using this product
■Do not take more than 9 tablets in 24-hours period or use the maximum dosage of this product for more than 2 weeks, except under the advice and supervision of a physician.

PREGNANCY OR BREAST FEEDING

If pregnant or breast-feeding, ask a health professional before use.

Keep out of reach of children.

Directions
■Adults and children 12 years of age and over: Take 3 tablets with water 3 times daily between meals and at bedtime, or as directed by a doctor.
■Children under 12 years: Ask a doctor.

Other information
■Each tablet contains: sodium 8 mg, magnesium 35 mg
■Do not purchase if printed seal with “sato” is broken or missing from top or bottom of carton.

INACTIVE INGREDIENT

Inactive ingredients caramel, colloidal silicon dioxide, croscarmellose sodium, flavor, hydroxypropyl cellulose, magnesium stearate, microcrystalline cellulose, synthetic iron oxide